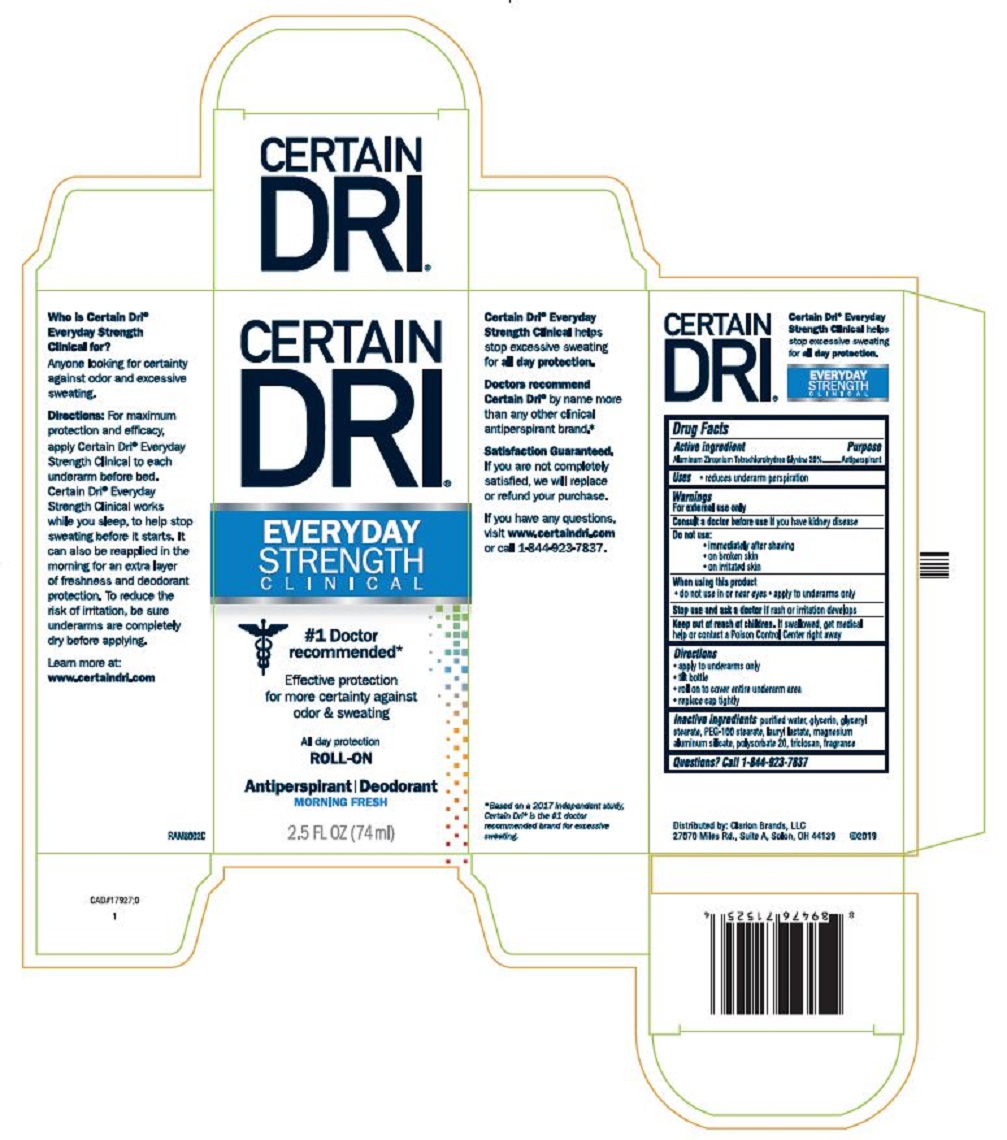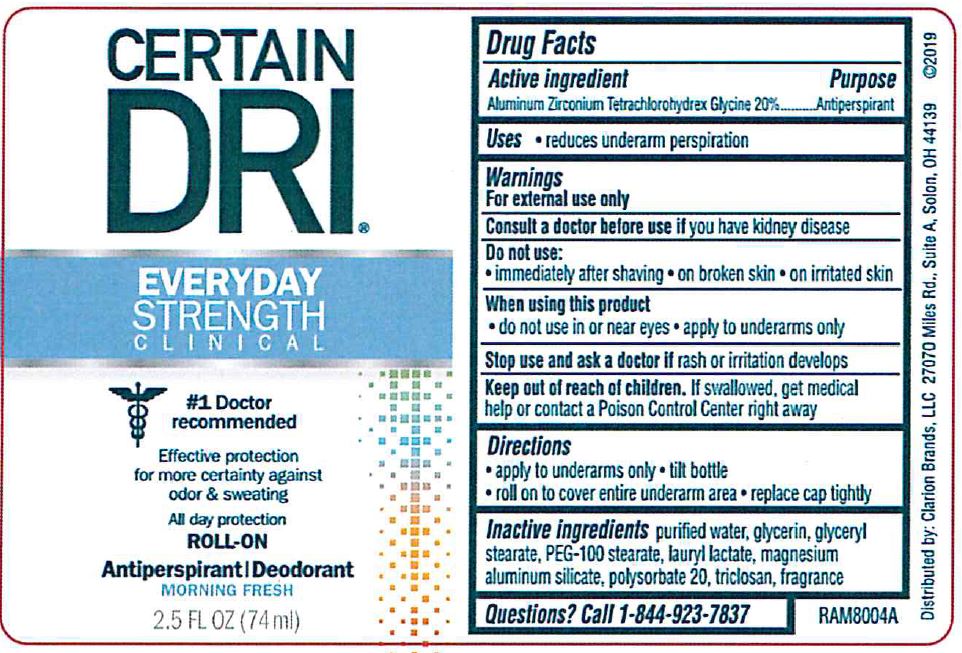 DRUG LABEL: CERTAIN DRI AM
NDC: 69693-718 | Form: LIQUID
Manufacturer: Clarion Brands, LLC
Category: otc | Type: HUMAN OTC DRUG LABEL
Date: 20251223

ACTIVE INGREDIENTS: ALUMINUM ZIRCONIUM TETRACHLOROHYDREX GLY 20 g/100 mL
INACTIVE INGREDIENTS: WATER; GLYCERIN; GLYCERYL MONOSTEARATE; PEG-100 STEARATE; MAGNESIUM ALUMINUM SILICATE; POLYSORBATE 20; TRICLOSAN; LAURYL LACTATE

Drug Facts

Active Ingredient | Purpose
Aluminum Zirconium Tetrachlorohydrex Glycine 20% | Antiperspirant

Uses

- reduces underarm perspiration

Warnings

For external use only

ASK DOCTOR

Consult a Doctor before use ifyou have kidney disease

Do not use:

- immediately after shaving
- on broken skin
- on irritated skin

When using this product

- do not use in or near eyes
- apply to underarms only

Stop use and ask a doctor ifrash or irritation develops

Keep out of reach of children.If swallowed, get medical help or contact a Poison Control Center right away

Directions

- apply to underarms only
- tilt bottle
- roll on to cover entire underarm area
- replace cap tightly

Inactive ingredients

purified water, glycerin, glyceryl stearate, PEG 100 stearate, lauryl lactate, magnesium aluminum silicate, polysorbate 20, triclosan, fragrance

Questions? Call 1-844-923-7837

PRINCIPAL DISPLAY PANEL

CERTAIN DRI®
EVERYDAY
STRENGTH
CLINICAL
#1 Doctor recommended*
Effective protection
for more certainty against
odor & sweating
All day protection
ROLL-ON
Antiperspirant | Deodorant
MORNING FRESH
2.5 FL OZ (74 ml)
Who is Certain Dri®Everyday Strength Clinical for?
Anyone looking for certainty against odor and excessive sweating.
Directions:For maximum protection and efficacy, apply Certain Dri®Everyday Strength Clinical to each underarm before bed. Certain Dri®Everyday Strength Clinical works while you sleep, to help stop sweating before it starts. It can also be reapplied in the morning for an extra layer of freshness and deodorant protection. To reduce the risk of irritation, be sure underarms are completely dry before applying.
Learn more at:
www.certaindri.com
RAM8002C
Certain Dri®Everyday Strength Clinical helps stop excessive sweating for all day protection.
Doctors recommend Certain Dri® by name more than any other clinical antiperspirant brand.*
Satisfaction Guaranteed.
If you are not completely satisfied, we will replace or refund your purchase.
If you have any questions, visit www.certaindri.comor call 1-844-923-7837.
* Based on a 2017 independent study, Certain Dri®is the #1 doctor recommended brand for excessive sweating.
Certain Dri® Everyday Strength Clinicalhelps stop excessive sweating for all day protection.
Distributed by: Clarion Brands, LLC
27070 Miles Rd., Suite A, Solon, OH 44139 ©2019

CERTAIN DRI®
EVERYDAY
STRENGTH
CLINICAL
#1 Doctor
recommended
Effective protection
for more certainty against
odor & sweating
All day protection
ROLL-ON
Antiperspirant | Deodorant
MORNING FRESH
2.5 FL OZ (74 ml)
Distributed by: Clarion Brands, LLC 27070 Miles Rd., Suite A, Solon, OH 44139 ©2019
RAM8004A